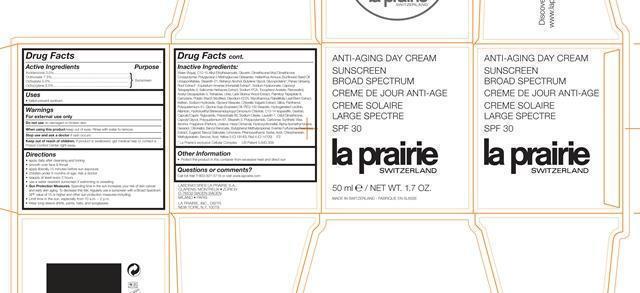 DRUG LABEL: Anti-Aging Day Broad Spectrum SPF 30
NDC: 68807-316 | Form: CREAM
Manufacturer: Temmentec AG
Category: otc | Type: HUMAN OTC DRUG LABEL
Date: 20170105

ACTIVE INGREDIENTS: AVOBENZONE 3 g/100 kg; OCTINOXATE 7.5 g/100 kg; OCTISALATE 5 g/100 kg; OCTOCRYLENE 2.5 g/100 kg
INACTIVE INGREDIENTS: WATER; GLYCERIN; DIMETHICONE/VINYL DIMETHICONE CROSSPOLYMER (SOFT PARTICLE); STEARETH-21; DOCOSANOL; BUTYLENE GLYCOL; ASIAN GINSENG; HYALURONATE SODIUM; SALICORNIA EUROPAEA; SODIUM PYRROLIDONE CARBOXYLATE; .ALPHA.-TOCOPHEROL ACETATE; RESVERATROL; TREHALOSE; UREA; LARIX SIBIRICA WOOD; CARNOSINE; EDETATE DISODIUM; MYROTHAMNUS FLABELLIFOLIA LEAF; SODIUM HYDROXIDE; GLYCERYL MONOSTEARATE; CHLORELLA VULGARIS; SILICON DIOXIDE; PANTHENOL; POLYQUATERNIUM-51 (2-METHACRYLOYLOXYETHYL PHOSPHORYLCHOLINE/N-BUTYL METHACRYLATE; 3:7); SOYBEAN OIL; PEG-100 STEARATE; HYDROGENATED SOYBEAN LECITHIN; ALLANTOIN; HYDROXYETHYL BEHENAMIDOPROPYL DIMONIUM CHLORIDE; C13-14 ISOPARAFFIN; MEDIUM-CHAIN TRIGLYCERIDES; POLYSORBATE 80; SODIUM OLEATE; LAURETH-7; CETYL DIMETHICONE 25; CAPRYLYL GLYCOL; STEARETH-2; POLYACRYLAMIDE (1500 MW); CARBOMER 934; SYNTHETIC WAX (1800 MW); ALCOHOL; LINALOOL, (+/-)-; .ALPHA.-HEXYLCINNAMALDEHYDE; HYDROXYCITRONELLAL; ISOMETHYL-.ALPHA.-IONONE; GERANIOL; .BETA.-CITRONELLOL, (R)-; BENZYL BENZOATE; BUTYLPHENYL METHYLPROPIONAL; PSEUDEVERNIA FURFURACEA; EUGENOL; BENZYL SALICYLATE; LIMONENE, (+)-; PHENOXYETHANOL; SORBIC ACID; CHLORPHENESIN; METHYLPARABEN; BENZOIC ACID; FD&C YELLOW NO. 5; FD&C RED NO. 4

Anti-Aging Day Cream SPF 30

Active ingredients purpose

Avobenzone 3.0% Sunscreen

Octinoxate 7.5% Sunscreen

Octisalate 5.0% Sunscreen

Octocrylene 2.5% Sunscreen

Uses

- helps prevent sunburn

Keep out of reach of children. If product is swallowed, get medical help or contact a Poison Control Center right away.

Stop use and ask a doctor if rash occurs.

Warnings

For external use only

Do not use on damaged or broken skin

When using this product keep out of eyes. Rinse with water to remove.

Directions

• apply daily after cleansing and toning

• smooth over face & throat

• apply liberally 15 minutes before sun exposure

• children under 6 months of age: Ask a doctor

• reapply at least every 2 hours

• use a water resistant sunscreen if swimming or sweating

Sun Protection Measures.

Spending time in the sun increases your risk of skin cancer

and early skin aging. To decrease this risk, regularly use a sunscreen with a Broad Spectrum

SPF value of 15 or higher and other sun protection measures including:

• Limit time in the sun, especially from 10 a.m. – 2 p.m.

• Wear long-sleeve shirts, pants, hats, and sunglasses

INACTIVE INGREDIENT

Water (Aqua), C12-15 Alkyl Ethylhexanoate, Glycerin, Dimethicone/Vinyl DimethiconeCrosspolymer, Polyglyceryl-3 Methylglucose Distearate, Helianthus Annuus (Sunflower) Seed Oil Unsaponifiables, Steareth-21, Behenyl Alcohol, Butylene Glycol, Glycoproteins, Panax Ginseng Root Extract, Equisetum Arvense (Horsetail) Extract, Sodium Hyaluronate, Caprooyl Tetrapeptide-3, Salicornia Herbacea Extract, Sodium PCA, Tocopheryl Acetate, Resveratrol, Acetyl Decapeptide-3, Trehalose, Urea, Larix Sibirica Wood Extract, Palmitoyl Tripeptide-8, Carnosine, Potato Starch Modified, Disodium EDTA, Myrothamnus Flabellifolia Leaf/Stem Extract, Kefiran, Sodium Hydroxide, Glyceryl Stearate, Chlorella Vulgaris Extract, Silica, Panthenol, Polyquaternium-51, Glycine Soja (Soybean) Oil, PEG-100 Stearate, Hydrogenated Lecithin, Allantoin, Hydroxyethyl Behenamidopropyl Dimonium Chloride, C13-14 Isoparaffin, Dextran, Caprylic/Capric Triglyceride, Polysorbate 80, Sodium Oleate, Laureth-7, Cetyl Dimethicone, Caprylyl Glycol, Polyquaternium-67, Steareth-2, Polyacrylamide, Carbomer, Synthetic Wax, Alcohol, Fragrance (Parfum), Linalool, Hexyl Cinnamal, Hydroxycitronellal, Alpha-Isomethyl Ionone, Geraniol, Citronellol, Benzyl Benzoate, Butylphenyl Methylpropional, Evernia Furfuracea (Treemoss) Extract, Eugenol, Benzyl Salicylate, Limonene, Phenoxyethanol, Sorbic Acid, Chlorphenesin, Methylparaben, Benzoic Acid, Yellow 5 (CI 19140), Red 4 (CI 14700)

PACKAGE LABEL

Anti-Aging Day Cream Sunscreen

Broad Spectrum

Creme De Jour Anti-Age Creme Solaire

Large Spectre

SPF 30

La Prairie Switerland

50 ml/ Net Wt. 1.7 Oz.